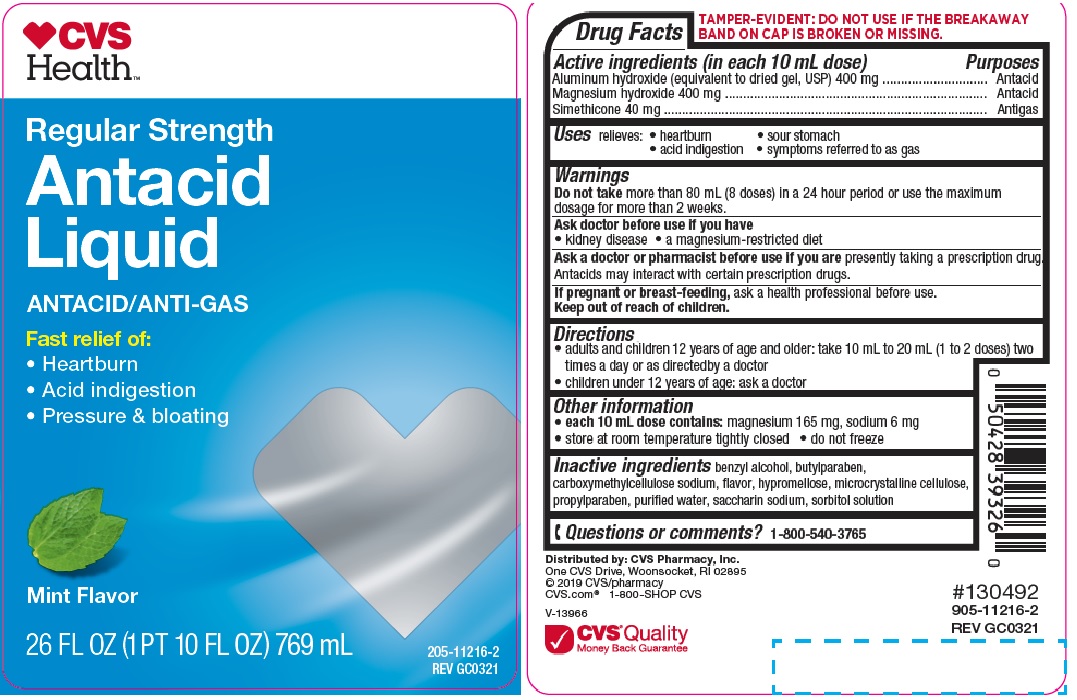 DRUG LABEL: REGULAR STRENGTH ANTACID MINT
NDC: 69842-355 | Form: LIQUID
Manufacturer: CVS
Category: otc | Type: HUMAN OTC DRUG LABEL
Date: 20241205

ACTIVE INGREDIENTS: ALUMINUM HYDROXIDE 400 mg/10 mL; MAGNESIUM HYDROXIDE 400 mg/10 mL; DIMETHICONE 40 mg/10 mL
INACTIVE INGREDIENTS: HYPROMELLOSES; CELLULOSE, MICROCRYSTALLINE; BUTYLPARABEN; PROPYLPARABEN; WATER; SACCHARIN SODIUM; SORBITOL SOLUTION; CARBOXYMETHYLCELLULOSE SODIUM; BENZYL ALCOHOL

CVS ANTACID MINT

Active ingredients (in each 10 mL dose)

Aluminum hydroxide 400 mg (equivalent to dried gel, USP)
Magnesium hydroxide 400 mg
Simethicone 40 mg

Purposes

Antacid

Antigas

Uses

relieves

- heartburn
- sour stomach
- acid indigestion
- the symptoms referred to as gas

Warnings

Do not take more than 80 mL (8 doses) in a 24 hour period or use the maximum
dosage for more than 2 weeks.

Ask a doctor before use if you have

• kidney disease
• a magnesium-restricted diet

Ask a doctor or pharmacist before use if you are presently taking a

prescription drug. Antacids may interact with certain prescription drugs.

If pregnant or breast-feeding, ask a health professional before use.

Keep out of reach of children.

Directions

- adults and children 12 years of age and older: take 10 mL to 20 mL (1 to 2 doses) two times a day or as directedby a doctor
- children under 12 years of age: ask a doctor

Other information

- each 10 mL dose contains: magnesium 165 mg, sodium 6 mg
- store at room temperature tightly closed
- do not freeze

Inactive ingredients

benzyl alcohol, butylparaben, carboxymethylcellulose sodium, flavor, hypromellose, microcrystalline cellulose, propylparaben, purified water, saccharin sodium, sorbitol solution

Questions or comments?

1-800-540-3765